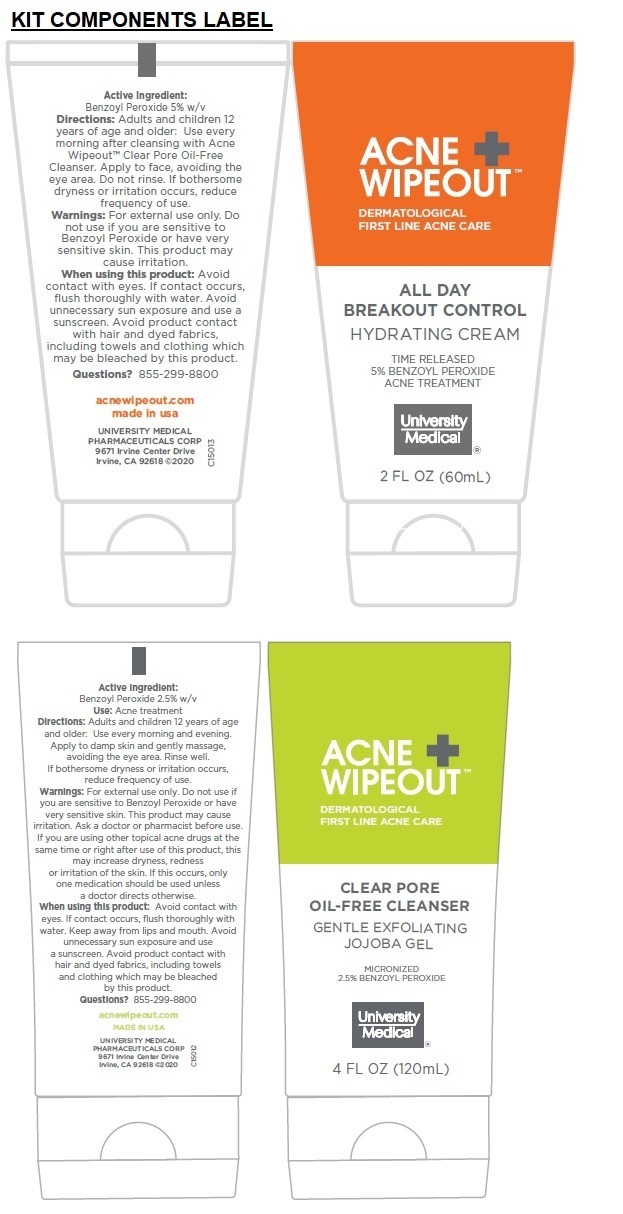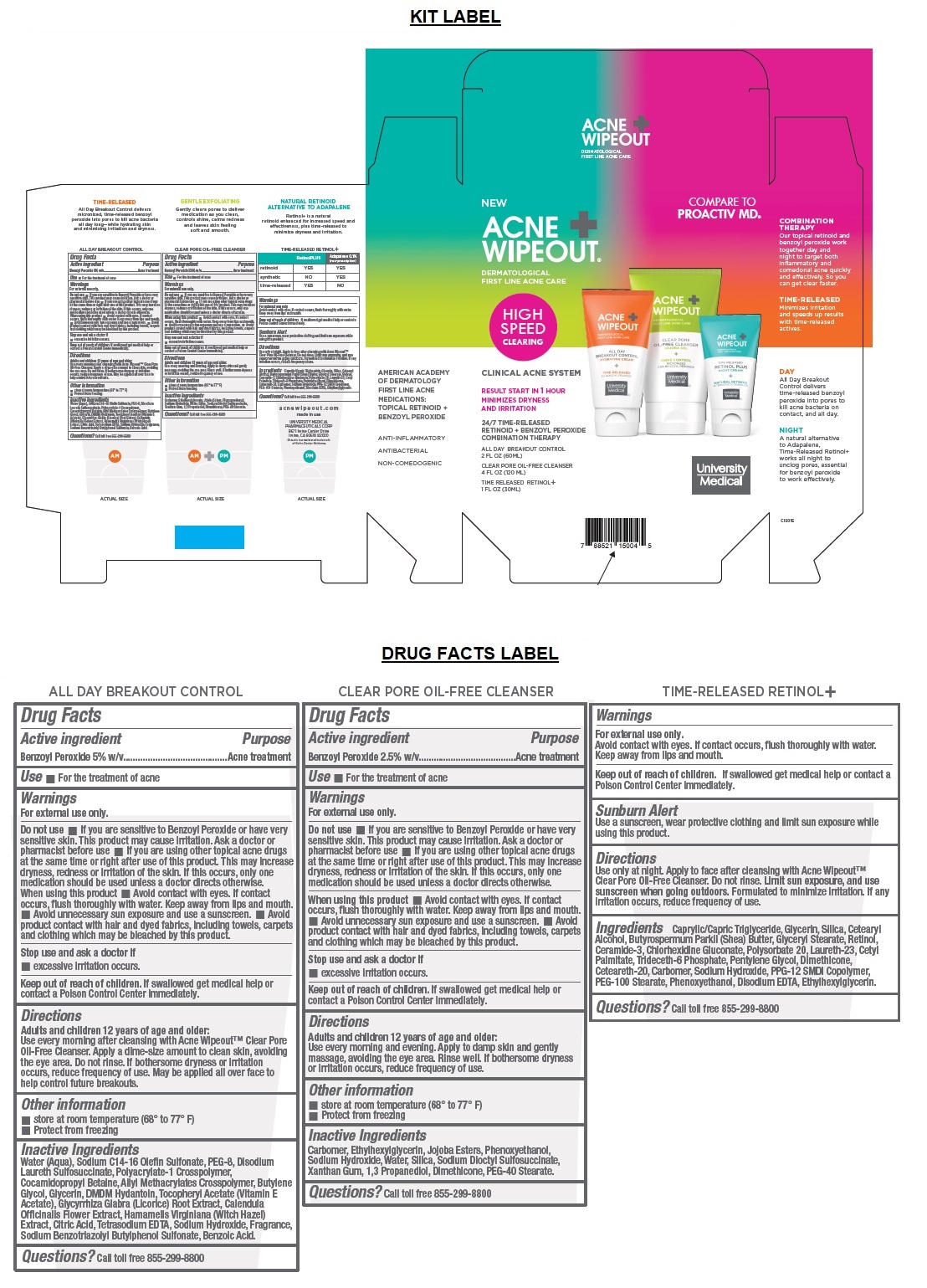 DRUG LABEL: ACNE WIPEOUT CLINICAL ACNE System
NDC: 50544-150 | Form: KIT | Route: TOPICAL
Manufacturer: University Medical Pharmaceuticals Corp.
Category: otc | Type: HUMAN OTC DRUG LABEL
Date: 20201015

ACTIVE INGREDIENTS: BENZOYL PEROXIDE 5 g/100 mL; BENZOYL PEROXIDE 2.5 g/100 mL
INACTIVE INGREDIENTS: WATER; SODIUM C14-16 OLEFIN SULFONATE; POLYETHYLENE GLYCOL 400; DISODIUM LAURETH SULFOSUCCINATE; CARBOMER HOMOPOLYMER, UNSPECIFIED TYPE; COCAMIDOPROPYL BETAINE; ALLYL METHACRYLATE/GLYCOL DIMETHACRYLATE CROSSPOLYMER; BUTYLENE GLYCOL; GLYCERIN; DMDM HYDANTOIN; .ALPHA.-TOCOPHEROL ACETATE; GLYCYRRHIZA GLABRA; CALENDULA OFFICINALIS FLOWER; HAMAMELIS VIRGINIANA TOP; CITRIC ACID MONOHYDRATE; EDETATE SODIUM; SODIUM HYDROXIDE; SODIUM BENZOTRIAZOLYL BUTYLPHENOL SULFONATE; BENZOIC ACID; CARBOMER HOMOPOLYMER, UNSPECIFIED TYPE; ETHYLHEXYLGLYCERIN; JOJOBA OIL; PHENOXYETHANOL; SODIUM HYDROXIDE; WATER; SILICON DIOXIDE; DOCUSATE SODIUM; XANTHAN GUM; PROPANEDIOL; DIMETHICONE; PEG-40 STEARATE

ACNE WIPEOUT® CLINICAL ACNE SYSTEM

ACNE WIPEOUT ALL DAY BREAKOUT CONTROL

Drug Facts

Active ingredient

Benzoyl Peroxide 5% w/v

Purpose

Acne treatment

Use

• For the treatment of acne

Warnings

For external use only.

Do not use • If you are sensitive to Benzoyl Peroxide or have very sensitive skin. This product may cause irritation. Ask a doctor or pharmacist before use • If you are using other topical acne drugs at the same time or right after use of this product. This may increase dryness, redness or irritation of the skin. If this occurs, only one medication should be used unless a doctor directs otherwise.
When using this product • Avoid contact with eyes. If contact occurs, flush thoroughly with water. Keep away from lips and mouth. • Avoid unnecessary sun exposure and use a sunscreen. • Avoid product contact with hair and dyed fabrics, including towels, carpets and clothing which may be bleached by this product.

Stop use and ask a doctor if
• if excessive irritation occurs.

Keep out of reach of children. If swallowed get medical help or contact a Poison Control Center immediately.

Directions

Adults and children 12 years of age and older:
Use every morning after cleansing with Acne Wipeout™ Clear Pore Oil-Free Cleanser. Apply a dime-size amount to clean skin, avoiding the eye area. Do not rinse. If bothersome dryness or irritation occurs, reduce frequency of use.

Other information

• store at room temperature (68° to 77° F)
• Protect from freezing

Inactive Ingredients

Water (Aqua), Sodium C14-16 Olefin Sulfonate, PEG-8, Disodium Laureth Sulfosuccinate, Polyacrylate-1 Crosspolymer, Cocamidopropyl Betaine, Allyl Methacrylates Crosspolymer, Butylene Glycol, Glycerin, DMDM Hydantoin, Tocopheryl Acetate (Vitamin E Acetate), Glycyrrhiza Glabra (Licorice) Root Extract, Calendula Officinalis Flower Extract, Hamamelis Virginiana (Witch Hazel) Extract, Citric Acid, Tetrasodium EDTA, Sodium Hydroxide, Fragrance, Sodium Benzotriazolyl Butylphenol Sulfonate, Benzoic Acid.

Questions? Call toll free 855-299-8800

ACNE WIPEOUT CLEAR PORE OIL-FREE CLEANSER

Drug Facts

Active ingredient

Benzoyl Peroxide 2.5% w/v

Purpose

Acne treatment

Use

• For the treatment of acne

Warnings

For external use only.

Do not use • If you are sensitive to Benzoyl Peroxide or have very sensitive skin. This product may cause irritation. Ask a doctor or pharmacist before use • If you are using other topical acne drugs at the same time or right after use of this product. This may increase dryness, redness or irritation of the skin. If this occurs, only one medication should be used unless a doctor directs otherwise.

When using this product • Avoid contact with eyes. If contact occurs, flush thoroughly with water. Keep away from lips and mouth. • Avoid unnecessary sun exposure and use a sunscreen. • Avoid product contact with hair and dyed fabrics, including towels, carpets and clothing which may be bleached by this product.

Stop use and ask a doctor if
• excessive irritation occurs.

Keep out of reach of children. If swallowed get medical help or contact a Poison Control Center immediately.

Directions

Adults and children 12 years of age and older:
Use every morning and evening. Apply to damp skin and gently massage, avoiding the eye area. Rinse well. If bothersome dryness or irritation occurs, reduce frequency of use.

Other information

- store at room temperature (68° to 77° F)
- Protect from freezing

Inactive Ingredients

Carbomer, Ethylhexylglycerin, Jojoba Esters, Phenoxyethanol, Sodium Hydroxide, Water, Silica, Sodium Dioctyl Sulfosuccinate, Xanthan Gum, 1,3 Propanediol, Dimethicone, PEG-40 Stearate.

Questions? Call toll free 855-299-8800

Warnings

For external use only.

Avoid contact with eyes. If contact occurs, flush thoroughly with water. Keep away from lips and mouth.

Sunburn Alert

Use a sunscreen, wear protective clothing and limit sun exposure while using this product.

Keep out of reach of children. If swallowed get medical help or contact a Poison Control Center immediately.

Directions

Use only at night. Apply to face after cleansing with Acne Wipeout™ Clear Pore Oil-Free Cleanser. Do not rinse. Limit sun exposure, and use sunscreen when going outdoors. Formulated to minimize irritation. If any irritation occurs, reduce frequency of use.

Ingredients

Caprylic/Capric Triglyeride, Glycerin, Silica, Cetearyl Alcohol, Butyrospermum Parkii (Shea) Butter, Glyceryl Stearate, Retinol, Ceramide-3, Chlorhexidine Gluconate, polysorbate 20, Laureth-23, Cetyl Palmitate, Tridecth-6 Phosphate, Pentylene Glycol, Dimethicone, Ceteareth-20, Carbomer, Sodium Hydroxide, PPG-12 SMDI Copolymer, PEG-100 Stearate, Phenoxyethanol, Disodium EDTA, Ethylhexylglycerin

Questions? call toll free 855-299-8800

DERMATOLOGICAL FIRST LINE ACNE CARE

HIGH SPEED CLEARING

RESULT START IN 1 HOUR MINIMIZES DRYNESS AND IRRITATION

24/7 TIME-RELEASED RETINOID + BENZOYL PEROXIDE COMBINATION THERAPY

ALL DAY BREAKOUT CONTROL 2 FL OZ (60ML)

CLEAR PORE OIL-FREE CLEANSER 4 FL OZ (120 ML)

TIME RELEASED RETINOL+ 1 FL OZ (30ML)

AMERICAN ACADEMY OF DERMATOLOGY FIRST LINE ACNE MEDICATIONS TOPICAL RETINOID + BENZOYL PEROXIDE

ANTI-INFLAMMATORY

ANTIBACTERIAL

NON-COMEDOGENIC

COMPARE TO PROACTIV MD®

COMBINATION THERAPY

Our topical retinoid and benzoyl peroxide work together day and night to target both inflammatory and comedonal acne quickly and effectively. So you can get clear faster.

TIME-RELEASED
Minimizes irritation and speeds up results with time-released actives.

DAY

All Day Breakout Control delivers time-released benzoyl peroxide into pores to kill acne bacteria on contact, and all day.

NIGHT

A natural alternative to Adapalene, Time-Released Retinol+ works all night to unclog pores, essential for benzoyl peroxide to work effectively.

TIME-RELEASED

All Day Breakout Control delivers micronized, time-released benzoyl peroxide into pores to kill acne bacteria all day long—while hydrating skin and minimizing irritation and dryness.

GENTLE EXFOLIATING

Gently clears pores to deliver medication as you clean, controls shine, calms redness and leaves skin feeling soft and smooth.

NATURAL RETINOID ALTERNATIVE TO ADAPALENE

Retinol+ is a natural retinoid enhanced for increased speed and effectiveness, plus time-released to minimize dryness and irritation.

acnewipeout.com

made in usa

UNIVERSITY MEDICAL

PHARMACEUTICALS CORP

9671 Irvine Center Drive

Irvine, CA 92618 ©2020

Proactiv is a registered trademark of Guthy-Renker Galderma.